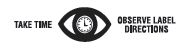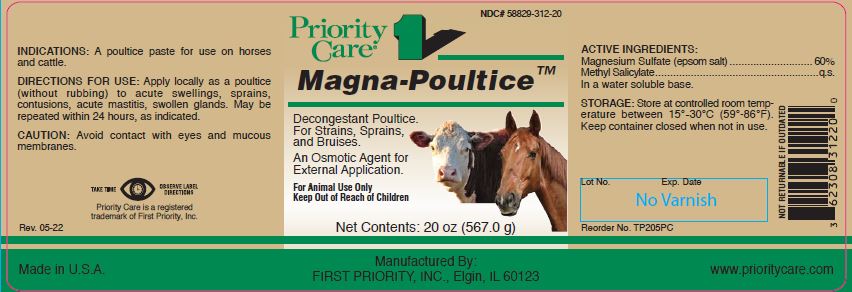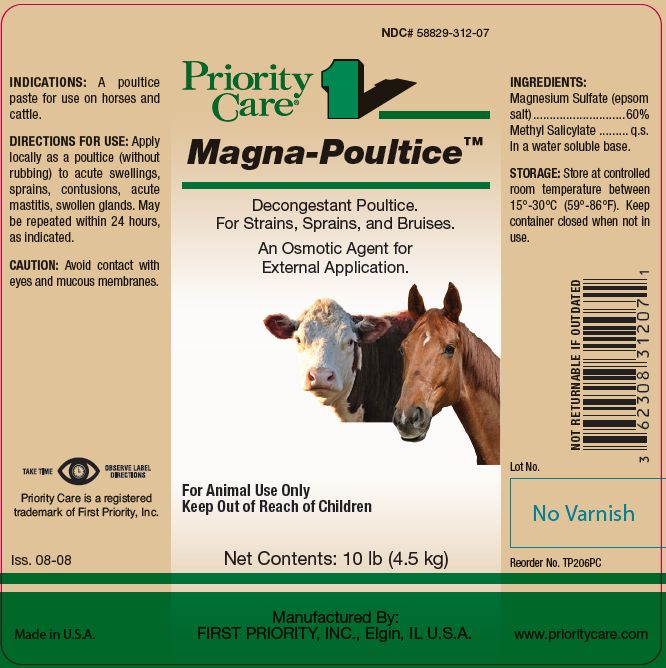 DRUG LABEL: Magna Poultice
NDC: 58829-312 | Form: POULTICE
Manufacturer: FIRST PRIORITY INCORPORATED
Category: animal | Type: OTC ANIMAL DRUG LABEL
Date: 20241028

ACTIVE INGREDIENTS: MAGNESIUM SULFATE HEPTAHYDRATE 600.5 mg/1 g; METHYL SALICYLATE 10 mg/1 g

Magna-Poultice™

PURPOSE

Decongestant Poultice.

For Strains, Sprains, and Bruises.

An Osmotic Agent for External Application.

KEEP OUT OF REACH OF CHILDREN

For Animal Use Only
Keep Out of Reach of Children

INDICATIONS:

A poultice paste for use on horses and cattle.

DIRECTIONS FOR USE:

Apply locally as a poultice (without rubbing) to acute swellings, sprains, contusions, acute mastitis, swollen glands. May be repeated within 24 hours, as indicated.

CAUTION:

Avoid contact with eyes and mucous membranes.

INGREDIENTS:

Magnesium Sulfate (epsom salt)...............60%
Methyl Salicylate ........................................ q.s.

INACTIVE INGREDIENT

In a water soluble base.

STORAGE:

Store at controlled room temperature between 15°-30°C (59°-86°F). Keep container closed when not in use.

Net Contents:

20 oz (567.0 g) Reorder No. TP205PC

10 lb (4.5 kg) Reorder No. TP206PC

INFORMATION FOR OWNERS/CAREGIVERS

Priority Care is a registered trademark of First Priority, Inc.

Made in U.S.A.

Manufactured By: FIRST PRIORITY, INC., Elgin, IL 60123

www.prioritycare.com

NOT RETURNABLE IF OUTDATED